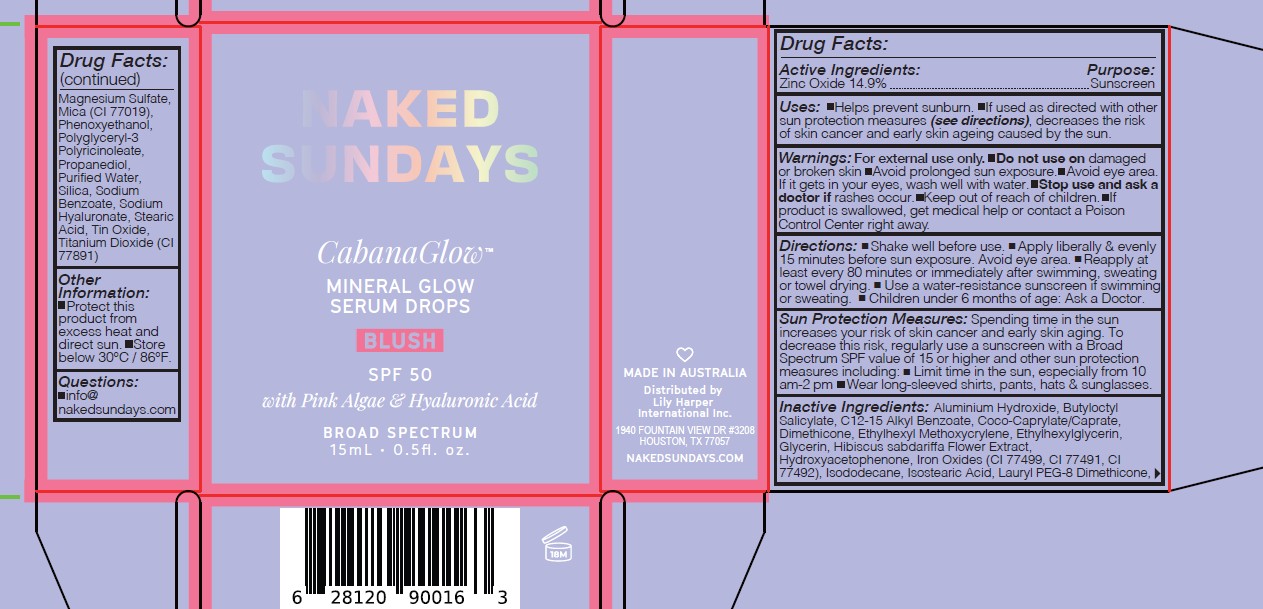 DRUG LABEL: NAKED SUNDAYS CABANA GLOW MINERAL GLOW SERUM DROPS Blush 40mL
NDC: 81104-257 | Form: LIQUID
Manufacturer: NAKED SUNDAYS PTY LTD
Category: otc | Type: HUMAN OTC DRUG LABEL
Date: 20250812

ACTIVE INGREDIENTS: ZINC OXIDE 14.9 g/100 mL
INACTIVE INGREDIENTS: CI 77891; SODIUM BENZOATE; GLYCERIN; DIMETHICONE; ETHYLHEXYLGLYCERIN; ALUMINUM HYDROXIDE; ETHYLHEXYL METHOXYCRYLENE; FERRIC OXIDE RED; ISOSTEARIC ACID; WATER; PROPANEDIOL; HYDROXYACETOPHENONE; PHENOXYETHANOL; HIBISCUS SABDARIFFA FLOWER; HYALURONATE SODIUM; LAURYL PEG-8 DIMETHICONE (300 CPS); MICA; ALKYL (C12-15) BENZOATE; MAGNESIUM SULFATE ANHYDROUS; POLYGLYCERYL-3 PENTARICINOLEATE; STEARIC ACID; COCO-CAPRYLATE/CAPRATE; ISODODECANE; CI 77499; CI 77492; TIN OXIDE; SILICA; BUTYLOCTYL SALICYLATE

NAKED SUNDAYS CABANA GLOW MINERAL GLOW SERUM DROPS Blush

ACTIVE INGREDIENTS

Zinc Oxide 14.9%

Purpose

Sunscreen

USES

Uses: Helps prevent sunburn. If used as
directed with other sun protection measures
(see directions), decreases the risk of skin
cancer and early skin ageing caused by the sun.

WARNINGS

Warnings: For external use only. Do not use
on damaged or broken skin Avoid prolonged
sun exposure. If it gets in your eyes, wash well
with water. Keep out of reach of children.
Stop use and ask a doctor if rashes occur.
If product is swallowed, get medical help or
contact a Poison Control Center right away.

Keep out of reach of children. If product is swallowed, get medical help or contact a Poison Control Center right away.

DIRECTIONS

- SPRAY 7 TIMES WITH MOUTH AND LIPS CLOSED 8-10" AWAY FROM FACE 15 MINUTES BEFORE SUN EXPOSURE.
- Reapply after 80 minutes of swimming or sweating.
- Reapply immediately after towel drying.
- Reapply at least every 2 hours.
- Children under 3 years of age: Ask a doctor.

SUN PROTECTION MEASURES:

Spending time in the sun increases your risk of skin cancer and early skin aging. To decrease this risk, regularly use a sunscreen with a Broad Spectrum SPF value of 15 or higher and other sun protection measures including:

- Limit time in the sun, especially from 10.00AM - 2.00PM
- Wear long-sleeved shirts, pants, hats, and sunglasses

INACTIVE INGREDIENTS

Inactive Ingredients: Aluminium Hydroxide,
Butyloctyl Salicylate, C12-15 Alkyl Benzoate,
Coco-Caprylate/Caprate, Dimethicone, Ethylhexyl
Methoxycrylene, Ethylhexylglycerin, Hibiscus
sabdariffa Flower Extract, Hydroxyacetophenone,
Iron Oxides/(CI 77499, CI 77491, CI 77492),
Isododecane, Isostearic Acid, Lauryl PEG-8
Dimethicone, Magnesium Sulfate, Mica/CI 77019,
Phenoxyethanol, Polyglyceryl-3 Polyricinoleate,
Propanediol, Purified Water, Silica, Sodium
Hyaluronate, Stearic Acid, Tin Oxide, Titanium
dioxide/CI 77891

OTHER INFORMATION

Other Information: Protect this product
from excess heat and direct sun. Store below
30°C / 86°F.

USER SAFETY WARNINGS

Directions: Shake well before use.
Apply liberally and reapply every 80 minutes,
especially after swimming or towel drying.
Sun Protection Measures Spending time in
the sun increases your risk of skin cancer and
early skin aging. To decrease this risk, regularly
use a sunscreen with a Broad Spectrum SPF
value of 15 or higher and other sun protection
measures including: Limit lime in the sun,
especially from 10 am-2 pm Wear longsleeved
shirts, pants, hats, and sunglasses For
Children under 6 months of age ask a doctor

PURPOSE

Sunscreen